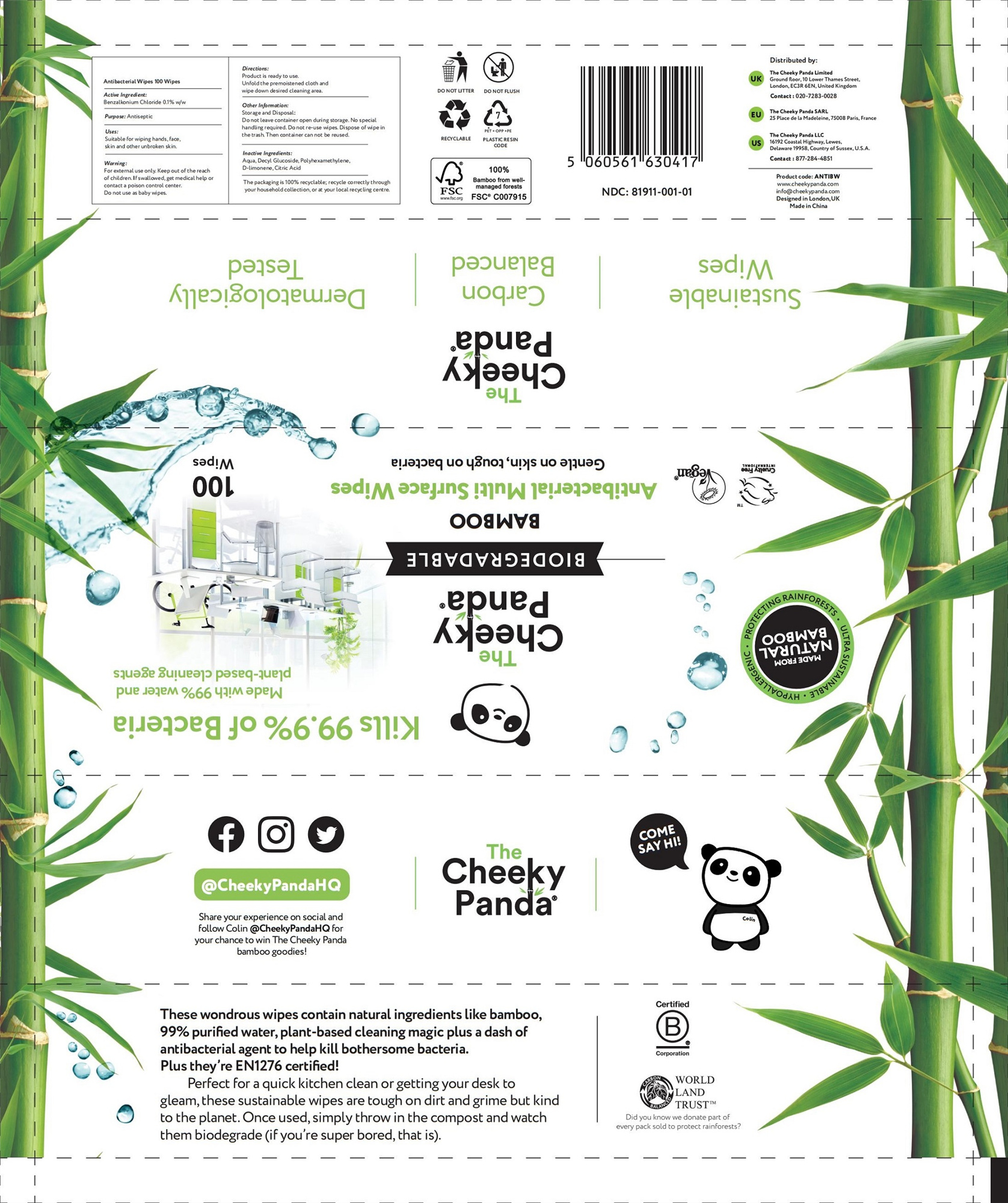 DRUG LABEL: BAMBOO Antibacterial Multi Surface Wipes
NDC: 81911-001 | Form: CLOTH
Manufacturer: THE CHEEKY PANDA LIMITED
Category: otc | Type: HUMAN OTC DRUG LABEL
Date: 20211219

ACTIVE INGREDIENTS: BENZALKONIUM CHLORIDE 0.1 g/100 g
INACTIVE INGREDIENTS: POLIHEXANIDE HYDROCHLORIDE; WATER; DECYL GLUCOSIDE; LIMONENE, (+/-)-; ANHYDROUS CITRIC ACID

BAMBOO Antibacterial Multi Surface Wipes

Active Ingredient

Benzalkonium Chloride 0.1% w/w

Purpose

Antiseptic

Uses

Suitable for wiping hands, face, skin and other unbroken skin.

Warning

For external use only. Keep out of the reach of children. If swallowed, get medical help or contact a poison control center.

Do not use as baby wipes.

Directions

Product is ready to use.

Unfold the premoistened cloth and wipe down desired cleaning area.

Keep out of the reach of children.

Other Information

Storage and Disposal:

Do not leave container open during storage. No special handling required. Do not re-use wipes. Dispose of wipe in the trash. Then container can not be reused.

Inactive Ingredients

Aqua, Decyl Glucoside, Polyhexamethylene, D-limonene, Citric Acid

PACKAGE LABEL

100 Wipes, NDC: 81911-001-01